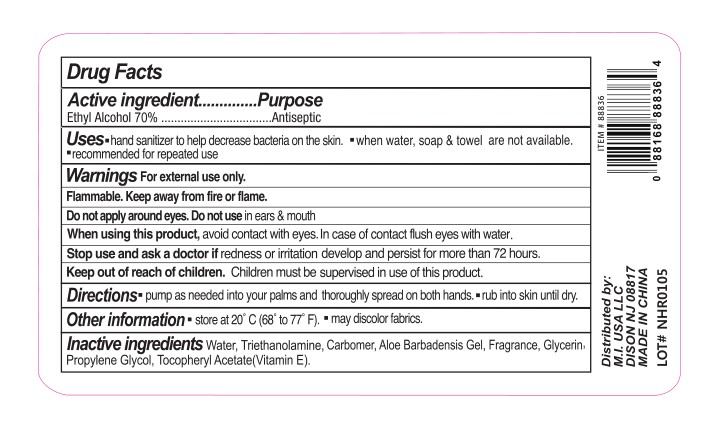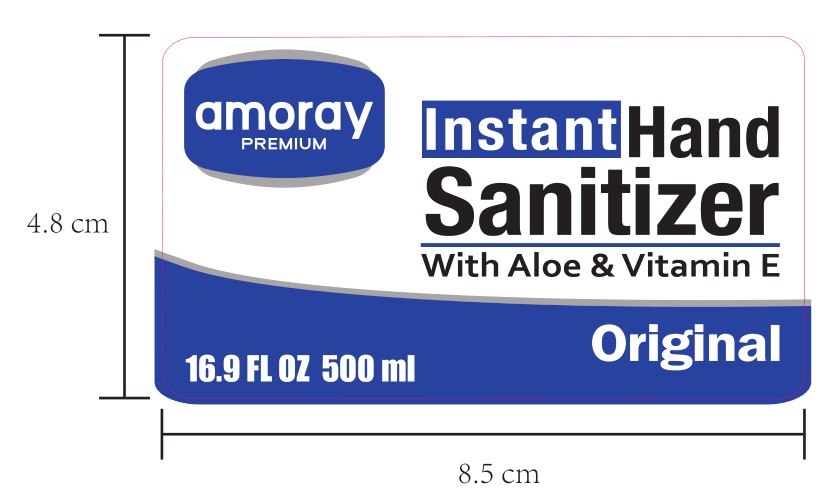 DRUG LABEL: AMORAY INSTANT  HAND SANITIZER
NDC: 75749-020 | Form: GEL
Manufacturer: NINGBO PRETTY TOURISM MANUFACTURE CO.,LTD.
Category: otc | Type: HUMAN OTC DRUG LABEL
Date: 20200709

ACTIVE INGREDIENTS: ALCOHOL 70 mL/100 mL
INACTIVE INGREDIENTS: GLYCERIN; ALOE; WATER; TROLAMINE; 1,2-PROPANEDIOL, 1-BENZOATE; .ALPHA.-TOCOPHEROL ACETATE; CARBOMER HOMOPOLYMER, UNSPECIFIED TYPE

Active ingredient

Ethyl Alcohol 70%

Purpose

Antiseptic

Uses

- hand sanitizer to help decrease bacteria on the skin
- when water, soap & towel are not available.
- recommended for repeated use

Warnings

For external use only. Flammable. Keep away from fire or flame.

Do not use

Do not apply around eyes. Do not use in ears & mouth.

When using this product, avoid contact with eyes. In case of contact flush eyes with water.

Stop use and ask a doctor if redness or irritation develop and persist for more than 72 hours.

Keep out of reach of children

Children must be supervised in use of this product.

Directions

- pump as needed into your palms and thoroughly spread on both hands
- rub into skin until dry.

Other information

- store at 20 C (68 to77 F)
- may discolor fabrics

Inactive ingredients

Water,

Triethanolamine,

Carbomer,

Aloe Barbadensis Gel

Fragrance,

Glycerin,

Propylene Glycol,

Tocopheryl Acetate (Vitamine E)